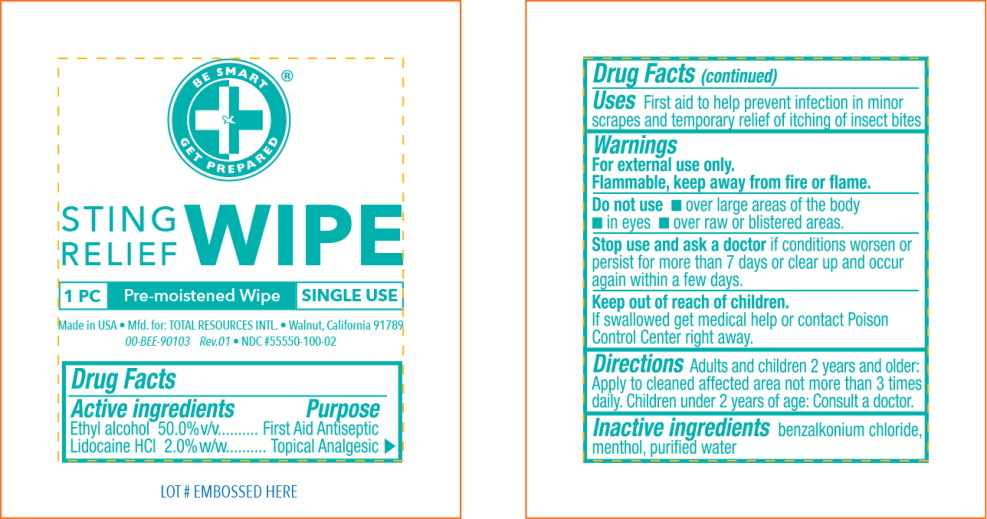 DRUG LABEL: Antiseptic
NDC: 55550-100 | Form: LIQUID
Manufacturer: Total Resources International
Category: otc | Type: HUMAN OTC DRUG LABEL
Date: 20200114

ACTIVE INGREDIENTS: alcohol 500 mg/1 g; lidocaine hydrochloride 20 mg/1 g
INACTIVE INGREDIENTS: benzalkonium chloride; menthol; water

Drug Facts

Active ingredients

Ethyl alcohol 50.0% v/v

Lidocaine HCI 2.0% w/w

Purpose

First Aid Antiseptic

Topical Analgesic

Uses

First aid to help prevent infection in minor scrapes and temporary relief of itching of insect bites

Warnings

For external use only.

Flammable, keep away from fire or flame.

Do not use

- over large areas of the body
- in eyes
- over raw or blistered areas.

Stop use and ask a doctor if conditions worsen or persist for more than 7 days or clear up and occur again within a few days.

Keep out of reach of children.

If swallowed get medical help or contact Poison Control Center right away.

Directions

Adults and children 2 years and older: Apply to cleaned affected area not more than 3 times daily. Children under 2 years of age: Consult a doctor.

Inactive ingredients

benzalkonium chloride, menthol, purified water

Principal Display Panel – Pouch Label

BE SMART

GET PREPARED

STING
RELIEF WIPE

1 PC

Pre-moistened Wipe

SINGLE USE

Made in USA • Mfd. for: TOTAL RESOURCES INTL. • Walnut, California 91789

00-BEE-90103 Rev.01 • NDC #55550-100-02